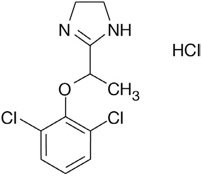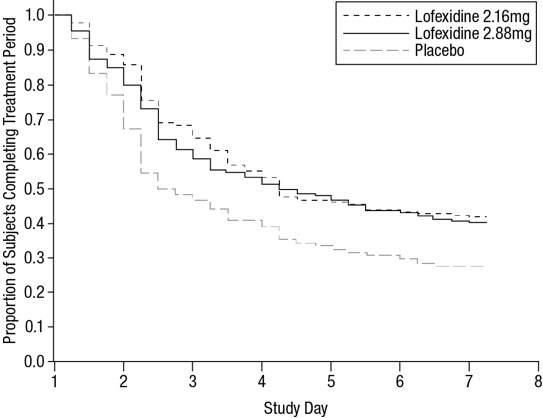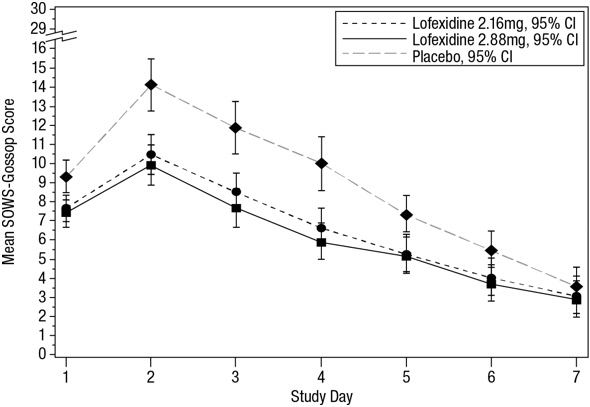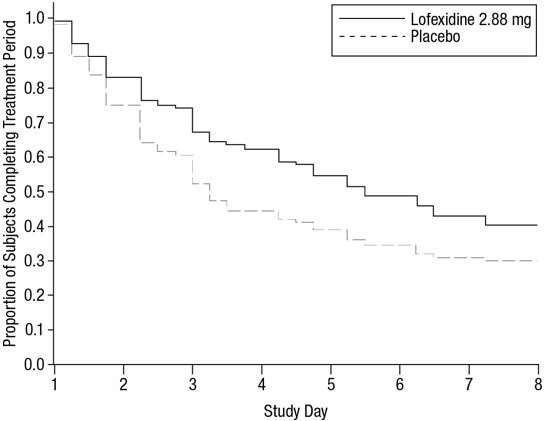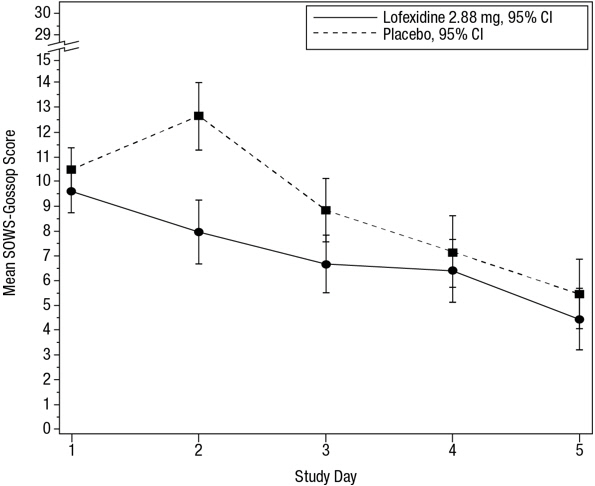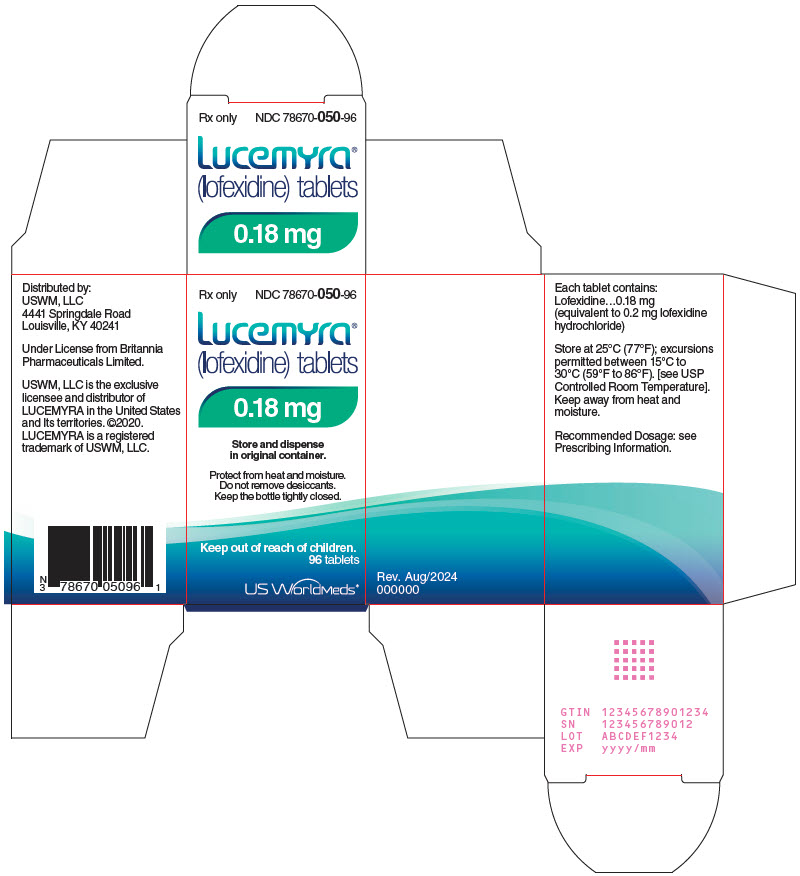 DRUG LABEL: Lucemyra
NDC: 78670-050 | Form: TABLET, FILM COATED
Manufacturer: USWM, LLC
Category: prescription | Type: HUMAN PRESCRIPTION DRUG LABEL
Date: 20260121

ACTIVE INGREDIENTS: LOFEXIDINE HYDROCHLORIDE 0.2 mg/1 1
INACTIVE INGREDIENTS: LACTOSE, UNSPECIFIED FORM; CITRIC ACID MONOHYDRATE; POVIDONE, UNSPECIFIED; MICROCRYSTALLINE CELLULOSE; CALCIUM STEARATE; SODIUM LAURYL SULFATE

HIGHLIGHTS OF PRESCRIBING INFORMATION

These highlights do not include all the information needed to use LUCEMYRA safely and effectively. See full prescribing information for LUCEMYRA.
LUCEMYRA® (lofexidine) tablets, for oral use
Initial U.S. Approval: 2018

1 INDICATIONS AND USAGE

LUCEMYRA is a central alpha-2 adrenergic agonist indicated for mitigation of opioid withdrawal symptoms to facilitate abrupt opioid discontinuation in adults. (1)

2 DOSAGE AND ADMINISTRATION

- The usual LUCEMYRA dosage is three 0.18 mg tablets taken orally 4 times daily at 5- to 6-hour intervals. LUCEMYRA treatment may be continued for up to 14 days with dosing guided by symptoms. (2.1)
- Discontinue LUCEMYRA with a gradual dose reduction over 2 to 4 days. (2.1)
- Hepatic or Renal Impairment: Dosage adjustments are recommended based on degree of impairment. (2.2, 2.3)

3 DOSAGE FORMS AND STRENGTHS

Tablets: 0.18 mg. (3)

4 CONTRAINDICATIONS

None. (4)

5 WARNINGS AND PRECAUTIONS

- Risk of Hypotension, Bradycardia, and Syncope: May cause a decrease in blood pressure, a decrease in pulse, and syncope. Monitor vital signs before dosing and advise patients on how to minimize the risk of these cardiovascular effects and manage symptoms, should they occur. Monitor symptoms related to bradycardia and orthostasis. When using in outpatients, ensure that patients are capable of self-monitoring for signs and symptoms. Avoid use in patients with severe coronary insufficiency, recent myocardial infarction, cerebrovascular disease, or chronic renal failure, as well as in patients with marked bradycardia. (5.1)
- Risk of QT Prolongation: LUCEMYRA prolongs the QT interval. Avoid use in patients with congenital long QT syndrome. Monitor ECG in patients with electrolyte abnormalities, congestive heart failure, bradyarrhythmias, hepatic or renal impairment, or in patients taking other medicinal products that lead to QT prolongation. (5.2)
- Increased Risk of CNS Depression with Concomitant use of CNS Depressant Drugs: LUCEMYRA potentiates the CNS depressant effects of benzodiazepines and may potentiate the CNS depressant effects of alcohol, barbiturates, and other sedating drugs. (5.3)
- Increased Risk of Opioid Overdose after Opioid Discontinuation: Patients who complete opioid discontinuation are at an increased risk of fatal overdose should they resume opioid use. Use in conjunction with a comprehensive management program for treatment of opioid use disorder and inform patients and caregivers of increased risk of overdose. (5.4)
- Risk of Discontinuation Symptoms: Instruct patients not to discontinue therapy without consulting their healthcare provider. When discontinuing therapy, reduce dose gradually. (5.5)

6 ADVERSE REACTIONS

Most common adverse reactions (incidence ≥ 10% and notably more frequent than placebo) are orthostatic hypotension, bradycardia, hypotension, dizziness, somnolence, sedation, and dry mouth. (6.1)

To report SUSPECTED ADVERSE REACTIONS, contact US WorldMeds at 1-833-LUCEMYRA or FDA at 1-800-FDA-1088 or www.fda.gov/ medwatch

7 DRUG INTERACTIONS

- Methadone: Methadone and LUCEMYRA both prolong the QT interval. ECG monitoring is recommended when used concomitantly. (7.1)
- Oral Naltrexone: Concomitant use may reduce efficacy of oral naltrexone. (7.2)
- CYP2D6 Inhibitors: Concomitant use of paroxetine resulted in increased plasma levels of LUCEMYRA. Monitor for symptoms of orthostasis and bradycardia with concomitant use of a CYP2D6 inhibitor. (7.4)

FULL PRESCRIBING INFORMATION

1 INDICATIONS AND USAGE

LUCEMYRA is indicated for mitigation of opioid withdrawal symptoms to facilitate abrupt opioid discontinuation in adults.

2 DOSAGE AND ADMINISTRATION

2.1 Dosing Information

The usual LUCEMYRA starting dosage is three 0.18 mg tablets taken orally 4 times daily during the period of peak withdrawal symptoms (generally the first 5 to 7 days following last use of opioid) with dosing guided by symptoms and side effects. There should be 5 to 6 hours between each dose. The total daily dosage of LUCEMYRA should not exceed 2.88 mg (16 tablets) and no single dose should exceed 0.72 mg (4 tablets).

LUCEMYRA treatment may be continued for up to 14 days with dosing guided by symptoms.

Discontinue LUCEMYRA with a gradual dose reduction over a 2- to 4-day period to mitigate LUCEMYRA withdrawal symptoms (e.g., reducing by 1 tablet per dose every 1 to 2 days) [see Warnings & Precautions (5.5)]. The LUCEMYRA dose should be reduced, held, or discontinued for individuals who demonstrate a greater sensitivity to LUCEMYRA side effects [see Warnings and Precautions (5.1), Adverse Reactions (6.1)]. Lower doses may be appropriate as opioid withdrawal symptoms wane.

LUCEMYRA can be administered in the presence or absence of food.

2.2 Dosage Recommendations for Patients with Hepatic Impairment

Recommended dosage adjustments based on the degree of hepatic impairment are shown in Table 1. [see Use in Specific Populations (8.6), Clinical Pharmacology (12.3)].

Table 1: Dosage Recommendations in Patients with Hepatic Impairment
 | Mild Impairment | Moderate Impairment | Severe Impairment
Child-Pugh score | 5-6 | 7-9 | > 9
Recommended dose | 3 tablets 4 times daily (2.16 mg per day) | 2 tablets 4 times daily (1.44 mg per day) | 1 tablet 4 times daily (0.72 mg per day)

2.3 Dosage Recommendations for Patients with Renal Impairment

Recommended dosage adjustments based on the degree of renal impairment are shown in Table 2. LUCEMYRA may be administered without regard to the timing of dialysis [see Use in Specific Populations (8.7), Clinical Pharmacology (12.3)].

Table 2: Dosage Recommendations in Patients with Renal Impairment
 | Moderate Impairment | Severe Impairment, End-Stage Renal Disease, or on Dialysis
Estimated GFR, mL/min/1.73 m^2 | 30-89.9 | < 30
Recommended dose | 2 tablets 4 times daily (1.44 mg per day) | 1 tablet 4 times daily (0.72 mg per day)

3 DOSAGE FORMS AND STRENGTHS

LUCEMYRA is available as round, peach-colored, film-coated tablets, imprinted with "LFX" on one side and "18" on the other side. Each tablet contains 0.18 mg lofexidine (equivalent to 0.2 mg of lofexidine hydrochloride).

4 CONTRAINDICATIONS

None.

5 WARNINGS AND PRECAUTIONS

5.1 Risk of Hypotension, Bradycardia, and Syncope

LUCEMYRA can cause a decrease in blood pressure, a decrease in pulse, and syncope [see Adverse Reactions (6.1), Clinical Pharmacology (12.2)]. Monitor vital signs before dosing. Monitor symptoms related to bradycardia and orthostasis.

Patients being given LUCEMYRA in an outpatient setting should be capable of and instructed on self-monitoring for hypotension, orthostasis, bradycardia, and associated symptoms. If clinically significant or symptomatic hypotension and/or bradycardia occur, the next dose of LUCEMYRA should be reduced in amount, delayed, or skipped.

Inform patients that LUCEMYRA may cause hypotension and that patients moving from a supine to an upright position may be at increased risk for hypotension and orthostatic effects. Instruct patients to stay hydrated, on how to recognize symptoms of low blood pressure, and on how to reduce the risk of serious consequences should hypotension occur (e.g., sit or lie down, carefully rise from a sitting or lying position). Instruct outpatients to withhold LUCEMYRA doses when experiencing symptoms of hypotension or bradycardia and to contact their healthcare provider for guidance on how to adjust dosing.

Avoid using LUCEMYRA in patients with severe coronary insufficiency, recent myocardial infarction, cerebrovascular disease, chronic renal failure, and in patients with marked bradycardia.

Avoid using LUCEMYRA in combination with medications that decrease pulse or blood pressure to avoid the risk of excessive bradycardia and hypotension.

5.2 Risk of QT Prolongation

LUCEMYRA prolongs the QT interval.

Avoid using LUCEMYRA in patients with congenital long QT syndrome.

Monitor ECG in patients with congestive heart failure, bradyarrhythmias, hepatic impairment, renal impairment, or patients taking other medicinal products that lead to QT prolongation (e.g., methadone). In patients with electrolyte abnormalities (e.g., hypokalemia or hypomagnesemia), correct these abnormalities first, and monitor ECG upon initiation of LUCEMYRA [see Dosing and Administration (2.1), Adverse Reactions (6.1), Special Populations (8.6, 8.7), Clinical Pharmacology (12.2)].

5.3 Increased Risk of Central Nervous System Depression with Concomitant use of CNS Depressant Drugs

LUCEMYRA potentiates the CNS depressive effects of benzodiazepines and can also be expected to potentiate the CNS depressive effects of alcohol, barbiturates, and other sedating drugs. Advise patients to inform their healthcare provider of other medications they are taking, including alcohol.

Advise patients using LUCEMYRA in an outpatient setting that, until they learn how they respond to LUCEMYRA, they should be careful or avoid doing activities such as driving or operating heavy machinery.

5.4 Increased Risk of Opioid Overdose after Opioid Discontinuation

LUCEMYRA is not a treatment for opioid use disorder. Patients who complete opioid discontinuation are likely to have a reduced tolerance to opioids and are at increased risk of fatal overdose should they resume opioid use. Use LUCEMYRA in patients with opioid use disorder only in conjunction with a comprehensive management program for the treatment of opioid use disorder and inform patients and caregivers of this increased risk of overdose.

5.5 Risk of Discontinuation Symptoms

Stopping LUCEMYRA abruptly can cause a marked rise in blood pressure. Symptoms including diarrhea, insomnia, anxiety, chills, hyperhidrosis, and extremity pain have also been observed with LUCEMYRA discontinuation. Instruct patients not to discontinue therapy without consulting their healthcare provider. When discontinuing therapy with LUCEMYRA, gradually reduce the dose [see Dosing and Administration (2.1)].

Symptoms related to discontinuation can be managed by administration of the previous LUCEMYRA dose and subsequent taper.

6 ADVERSE REACTIONS

The following serious adverse reactions are described elsewhere in labeling:

- Hypotension, Bradycardia, and Syncope [see Warnings and Precautions (5.1)]
- QT Prolongation [see Warnings and Precautions (5.2)]
- Central Nervous System Depression [see Warnings and Precautions (5.3)]
- Opioid Overdose [see Warnings and Precautions (5.4)]
- Discontinuation Symptoms [see Warnings and Precautions (5.5)]

6.1 Clinical Trials Experience

Because clinical trials are conducted under widely varying conditions, adverse reaction rates observed in the clinical trials of a drug cannot be directly compared to adverse reaction rates observed for another drug and may not reflect the rates observed in practice.

The safety of LUCEMYRA was supported by three randomized, double-blind, placebo-controlled clinical trials, an open-label study, and clinical pharmacology studies with concomitant administration of either methadone, buprenorphine, or naltrexone.

The three randomized, double-blind, placebo-controlled clinical trials enrolled 935 subjects dependent on short-acting opioids undergoing abrupt opioid withdrawal. Patients were monitored before each dose in an inpatient setting.

Table 3 presents the incidence, rounded to the nearest percent, of adverse events that occurred in at least 10% of subjects treated with LUCEMYRA and for which the incidence in patients treated with LUCEMYRA was greater than the incidence in subjects treated with placebo in a study that tested two doses of LUCEMYRA, 2.16 mg per day and 2.88 mg per day, and placebo. The overall safety profile in the combined dataset was similar.

Orthostatic hypotension, bradycardia, hypotension, dizziness, somnolence, sedation, and dry mouth were notably more common in subjects treated with LUCEMYRA than subjects treated with placebo.

Table 3: Adverse Reactions Reported by ≥10% of LUCEMYRA-Treated Patients and More Frequently than Placebo
Adverse Reaction | LUCEMYRA 2.16 mg [Assigned dose; mean average daily dose received was 79% of assigned dose due to dose-holds for out-of-range vital signs.] (%) N=229 | LUCEMYRA 2.88 mg (%) N=222 | Placebo (%) N=151
Insomnia | 51 | 55 | 48
Orthostatic Hypotension | 29 | 42 | 5
Bradycardia | 24 | 32 | 5
Hypotension | 30 | 30 | 1
Dizziness | 19 | 23 | 3
Somnolence | 11 | 13 | 5
Sedation | 13 | 12 | 5
Dry Mouth | 10 | 11 | 0

Other notable adverse reactions associated with the use of LUCEMYRA but reported in <10% of patients in the LUCEMYRA group included:

- Syncope: 0.9%, 1.4% and 0% for LUCEMYRA 2.16 mg/day and 2.88 mg/day and placebo, respectively
- Tinnitus: 0.9%, 3.2% and 0% for LUCEMYRA 2.16 mg/day and 2.88 mg/day and placebo, respectively

Blood pressure changes and adverse reactions after LUCEMYRA cessation

Elevations in blood pressure above normal values (≥140 mmHg systolic) and above a subject's pre-treatment baseline are associated with discontinuing LUCEMYRA, and peaked on the second day after discontinuation, as shown in Table 4. Blood pressure values were evaluated for 3 days following the last dose of a 5-day course of LUCEMYRA 2.88 mg/day.

Table 4: Blood Pressure Elevations after Stopping Treatment
 | Abrupt LUCEMYRA Discontinuation 2.88 mg (N = 134) |  | Placebo (N = 129)
 | N at risk | n (%) | N at risk | n (%)
Systolic Blood Pressure on Day 2 after Discontinuation
≥ 140 mmHg and ≥ 20 mmHg increase from baseline | 58 | 23 (39.7) | 37 | 6 (16.2)
≥ 170 mmHg and ≥ 20 mmHg increase from baseline | 58 | 5 (8.6) | 37 | 0

Blood pressure elevations of a similar magnitude and incidence were observed in a small number of patients (N=10) that had a one-day, 50% dose reduction prior to discontinuation.

After stopping treatment, subjects who were taking LUCEMYRA also had a higher incidence of diarrhea, insomnia, anxiety, chills, hyperhidrosis, and extremity pain compared to subjects who were taking placebo.

Sex-specific adverse event findings

Four out of 101 females (4%) had serious cardiovascular adverse events compared to 3 out of 289 (1%) males assigned to receive LUCEMYRA 2.88 mg/day.

Discontinuations and dose-holds due to bradycardia and orthostatic hypotension, which are the most common adverse reactions associated with LUCEMYRA, occurred with a greater incidence in females assigned to receive the highest studied dose of LUCEMYRA, 2.88 mg/day as shown in Table 5.

Table 5: Discontinuations and Dose-Holds for Bradycardia and Orthostatic Hypotension by LUCEMYRA Dose and Sex
 | LUCEMYRA 2.16 mg | LUCEMYRA 2.88 mg
Male | 22/162 (14%) | 29/158 (18%)
Female | 9/67 (13%) | 20/64 (31%)

6.2 Postmarketing Experience

Lofexidine is marketed in other countries for relief of opioid withdrawal symptoms. The following events have been identified during postmarketing use of lofexidine. Because these reactions are reported voluntarily from a population of uncertain size, it is not always possible to reliably estimate their frequency or establish a causal relationship to drug exposure.

Since lofexidine's initial market introduction in 1992, the most frequently reported postmarketing adverse event with lofexidine has been hypotension [see Warnings and Precautions (5.1)]. There has been one report of QT prolongation, bradycardia, torsades de pointes, and cardiac arrest with successful resuscitation in a patient who received lofexidine, and three reports of clinically significant QT prolongation in subjects concurrently receiving methadone with lofexidine.

7 DRUG INTERACTIONS

7.1 Methadone

LUCEMYRA and methadone both prolong the QT interval. ECG monitoring is recommended in patients receiving methadone and LUCEMYRA concomitantly [see Warnings and Precautions (5.2), Clinical Pharmacology (12.3)].

7.2 Oral Naltrexone

Coadministration of LUCEMYRA and oral naltrexone resulted in statistically significant differences in the steady-state pharmacokinetics of naltrexone. It is possible that oral naltrexone efficacy may be reduced if used concomitantly within 2 hours of LUCEMYRA. This interaction is not expected if naltrexone is administered by non-oral routes [see Clinical Pharmacology (12.3)].

7.3 CNS Depressant Drugs

LUCEMYRA potentiates the CNS depressant effects of benzodiazepines and may potentiate the CNS depressant effects of alcohol, barbiturates, and other sedating drugs. Advise patients to inform their healthcare provider of other medications they are taking, including alcohol [see Warnings and Precautions (5.3)].

7.4 CYP2D6 Inhibitor - Paroxetine

Coadministration of LUCEMYRA and paroxetine resulted in a 28% increase in the extent of absorption of LUCEMYRA. Monitor for orthostatic hypotension and bradycardia when an inhibitor of CYP2D6 is used concomitantly with LUCEMYRA [see Clinical Pharmacology (12.3)].

8 USE IN SPECIFIC POPULATIONS

8.1 Pregnancy

Risk Summary

The safety of LUCEMYRA in pregnant women has not been established. In animal reproduction studies, oral administration of lofexidine during organogenesis to pregnant rats and rabbits caused a reduction in fetal weights, increases in fetal resorptions, and litter loss at exposures below that in humans. When oral lofexidine was administered from the beginning of organogenesis through lactation, increased stillbirths and litter loss were noted along with decreased viability and lactation indices. The offspring exhibited delays in sexual maturation, auditory startle, and surface righting. These effects occurred at exposures below that in humans [see Animal Data].

The background risk of major birth defects and miscarriage for the indicated population is unknown. All pregnancies carry some risk of birth defect, loss, or other adverse outcomes. The background risk of major birth defects in the U.S. general population is 2% to 4% and of miscarriage is 15% to 20% of clinically recognized pregnancies.

Data

Animal Data

Increased incidence of resorptions, decreased number of implantations, and a concomitant reduction in the number of fetuses were observed when pregnant rabbits were orally administered lofexidine hydrochloride during organogenesis (from gestation day [GD] 7 to 19) at a daily dose of 5.0 mg/kg/day (approximately 0.08 times the maximum recommended human dose [MRHD] of 2.88 mg lofexidine base on an AUC basis). Maternal toxicity evidenced by increased mortality was noted at the highest tested dose of 15 mg/kg/day (approximately 0.4 times the MRHD on an AUC basis).

Decreased implantations per dam and decreased mean fetal weights were noted in a study in which pregnant rats were treated with oral lofexidine hydrochloride during organogenesis (from GD 7 to 16) at a daily dose of 3.0 mg/kg/day (approximately 0.9 times the MRHD on an AUC basis). This dose was associated with maternal toxicity (decreased body weight gain and mortality). No malformations or evidence of developmental toxicity were evident at 1.0 mg/kg/day (approximately 0.2 times the MRHD on an AUC basis).

A dose-dependent increase in pup mortality was noted in all doses of lofexidine hydrochloride administered orally to pregnant rats from GD 6 through lactation at an exposure less than the human exposure based on AUC comparisons. Doses higher than 1.0 mg/kg/day (approximately 0.2 times the MRHD on an AUC basis) resulted in incidences of total litter loss and maternal toxicity (piloerection and decreased body weight gain). At the highest dose tested of 2.0 mg/kg/day (approximately 0.6 times the MRHD on an AUC basis), increased stillbirths as well as decreased viability and lactation indices were reported. Surviving offspring exhibited lower body weights, developmental delays, and increased delays in auditory startle at doses of 1.0 mg/kg/ day or higher. Sexual maturation was delayed in male offspring (preputial separation) at 2.0 mg/kg/day and in female offspring (vaginal opening) at 1.0 mg/kg/day or higher.

8.2 Lactation

Risk Summary

There is no information regarding the presence of LUCEMYRA or its metabolites in human milk, the effects on the breastfed infant, or the effects on milk production. Caution should be exercised when LUCEMYRA is administered to a nursing woman.

The developmental and health benefits should be considered along with the mother's clinical need for LUCEMYRA and any other potential adverse effects on breastfed children from LUCEMYRA or from the underlying maternal condition.

8.3 Females and Males of Reproductive Potential

In animal studies that included some fertility endpoints, lofexidine decreased breeding rate and increased resorptions at exposures below human exposures. The impact of lofexidine on male fertility has not been adequately characterized in animal studies [see Impairment of Fertility (13.1)].

8.4 Pediatric Use

The safety and effectiveness of LUCEMYRA have not been established in pediatric patients.

8.5 Geriatric Use

No studies have been performed to characterize the pharmacokinetics of LUCEMYRA or to establish its safety and effectiveness in geriatric patients. Caution should be exercised when LUCEMYRA is administered to patients over 65 years of age. Dosing adjustments similar to those recommended in patients with renal impairment should be considered [see Dosage and Administration (2.3), Use in Specific Populations (8.7)].

8.6 Hepatic Impairment

Hepatic impairment slows the elimination of LUCEMYRA but exhibits less effect on the peak plasma concentration than on AUC values following a single dose. Dosage adjustments are recommended based on the degree of hepatic impairment. [see Dosage and Administration (2.2), Clinical Pharmacology (12.3)].

Clinically relevant QT prolongation may occur in subjects with hepatic impairment [see Warnings and Precautions (5.2), Clinical Pharmacology (12.2)].

8.7 Renal Impairment

Renal impairment slows the elimination of LUCEMYRA but exhibits less effect on the peak plasma concentration than on AUC values following a single dose. Dosage adjustments are recommended based on the degree of renal impairment [see Dosage and Administration (2.3), Clinical Pharmacology (12.3)].

Only a negligible fraction of the LUCEMYRA dose is removed during a typical dialysis session, so no additional dose needs to be administered after a dialysis session; LUCEMYRA may be administered without regard to the timing of dialysis [see Dosage and Administration (2.3), Clinical Pharmacology (12.3)].

Clinically relevant QT prolongation may occur in subjects with renal impairment [see Warnings and Precautions (5.2), Clinical Pharmacology (12.2)].

8.8 CYP2D6 Poor Metabolizers

Although the pharmacokinetics of LUCEMYRA have not been systematically evaluated in patients who do not express the drug metabolizing enzyme CYP2D6, it is likely that the exposure to LUCEMYRA would be increased similarly to taking strong CYP2D6 inhibitors (approximately 28%). Monitor adverse events such as orthostatic hypotension and bradycardia in known CYP2D6 poor metabolizers. Approximately 8% of Caucasians and 3 to 8% of Black/African Americans cannot metabolize CYP2D6 substrates and are classified as poor metabolizers (PM) [see Clinical Pharmacology (12.3)].

10 OVERDOSAGE

Overdose with LUCEMYRA may manifest as hypotension, bradycardia, and sedation. In the event of acute overdose, perform gastric lavage where appropriate. Dialysis will not remove a substantial portion of the drug. Initiate general symptomatic and supportive measures in cases of overdosage.

11 DESCRIPTION

LUCEMYRA tablets contain lofexidine, a central alpha-2 adrenergic agonist, as the hydrochloride salt. Lofexidine hydrochloride is chemically designated as 2-[1-(2,6-dichlorophenoxy)ethyl]-4,5 dihydro-1H- imidazole monohydrochloride with a molecular formula of C11H12Cl2N2O∙HCl. Its molecular weight is 295.6 g/mole and its structural formula is:

Lofexidine hydrochloride is a white to off-white crystalline powder freely soluble in water, methanol, and ethanol. It is slightly soluble in chloroform and practically insoluble in n-hexane and benzene.

LUCEMYRA is available as round, convex-shaped, peach-colored, film-coated tablets for oral administration. Each tablet contains 0.18 lofexidine, equivalent to 0.2 mg of lofexidine hydrochloride, and the following inactive ingredients: 92.6 mg lactose, 12.3 mg citric acid, 1.1 mg povidone, 5.7 mg microcrystalline cellulose, 1.4 mg calcium stearate, 0.7 mg sodium lauryl sulphate, and Opadry OY S 9480 (contains indigo carmine and sunset yellow).

12 CLINICAL PHARMACOLOGY

12.1 Mechanism of Action

Lofexidine is a central alpha-2 adrenergic agonist that binds to receptors on adrenergic neurons. This reduces the release of norepinephrine and decreases sympathetic tone.

12.2 Pharmacodynamics

Cardiac Electrophysiology

Single LUCEMYRA doses of 1.44 mg to 1.8 mg produced maximum mean change from baseline in QTcF (ΔQTcF) of 14.4 msec (upper two-sided 90% CI: 22.3 msec) and 13.6 msec (17.4 msec) for 1.44 mg and 1.8 mg respectively in healthy normal volunteers.

In a Phase 3 placebo-controlled, dose response study in opioid dependent subjects, LUCEMYRA was associated with a maximum mean prolongation of the QTcF interval 7.3 (8.8) msec and 9.3 (10.9) msec at doses of 2.16 mg/day and 2.88 mg/day, respectively.

Patients with hepatic impairment

Administration of LUCEMYRA to subjects with hepatic impairment was associated with prolongation of the QTc interval, which was more pronounced in subjects with severe hepatic impairment [see Use in Specific Populations (8.6)].

Patients with renal impairment

Administration of LUCEMYRA to subjects with renal impairment was associated with prolongation of the QTc interval, which was more pronounced in subjects with severe renal impairment [see Use in Specific Populations (8.7)].

LUCEMYRA coadministered with methadone

LUCEMYRA (2.88 mg/day) coadministered with methadone in 18 methadone-maintained patients (80 to 120 mg/day) resulted in a maximum mean increase from methadone-alone baseline in QTcF of 9.1 (14.2) msec.

LUCEMYRA coadministered with buprenorphine

LUCEMYRA (2.88 mg/day) coadministered with buprenorphine in 21 buprenorphine-maintained patients (16 to 24 mg/day) resulted in a maximum mean QTcF increase of 1.5 (5.6) msec compared to a buprenorphine-alone baseline.

In Vitro Binding

LUCEMYRA exhibits in vitro binding affinity and functional agonist activity with alpha-2A and alpha-2C adrenoreceptors at concentrations within clinical exposure plasma levels (Ki values of approximately 7.2 nM and 12 nM, and EC50 values of 4.9 nM and 0.9 nM, respectively).

12.3 Pharmacokinetics

Absorption

LUCEMYRA is well absorbed and achieves peak plasma concentration 3 to 5 hours after administration of a single dose.

LUCEMYRA shows approximately dose-proportional pharmacokinetics. Administration of LUCEMYRA with food does not alter its pharmacokinetics.

The absolute bioavailability of a single oral LUCEMYRA dose (0.36 mg in solution) compared with an intravenous infusion (0.2 mg infused for 200 minutes) was 72%. Mean LUCEMYRA Cmax after the oral dose and intravenous infusion was 0.82 ng/mL (at median Tmax of 3 hours) and 0.64 ng/mL (at median Tmax of 4 hours), respectively. Mean estimates of overall systemic exposure (AUCinf) were 14.9 ng∙h/mL and 12.0 ng∙h/mL, respectively.

Distribution

Mean LUCEMYRA apparent volume of distribution and volume of distribution values following the administration of an oral dose and an intravenous dose were 480.0 L and 297.9 L, respectively, which are appreciably greater than total body volume, suggesting extensive LUCEMYRA distribution into body tissue.

LUCEMYRA protein binding is approximately 55%.

LUCEMYRA is not preferentially taken up by blood cells. In a study comparing LUCEMYRA concentrations in plasma and whole blood at the time of peak LUCEMYRA concentrations in human volunteers, it was determined that red blood cells contain approximately 27% the LUCEMYRA concentration of the plasma.

Elimination

Metabolism

From absolute bioavailability results, approximately 30% of the administered LUCEMYRA dose is converted to inactive metabolites during the first pass effect associated with drug absorption from the gut.

LUCEMYRA and its major metabolites did not induce or inhibit any CYP450 isoforms, with the exception of a slight inhibition of CYP2D6 by LUCEMYRA, with an IC50 of 4551 nM (approximately 225 times the steady-state Cmax for LUCEMYRA with 0.72 mg 4 times daily dosing). Any LUCEMYRA interaction with CYP2D6 substrates is not expected to be clinically significant.

LUCEMYRA is metabolized when incubated in vitro with human liver microsomes, the major contributor to the hepatic metabolism of LUCEMYRA is CYP2D6, with CYP1A2 and CYP2C19 also capable of metabolizing LUCEMYRA.

Excretion

The elimination half-life is approximately 12 hours and mean clearance is 17.6 L/h following an IV infusion.

LUCEMYRA has a terminal half-life of approximately 11 to 13 hours following the first dose. At steady-state, the terminal half- life is approximately 17 to 22 hours. Accumulation occurs up to 4 days with repeat dosing, following the recommended dosing regimen.

A mass balance study of LUCEMYRA showed nearly complete recovery of radiolabel in urine (93.5%) over 144 hours postdose, with an additional 0.92% recovered in the feces over 216 hours postdose. Thus, it appears that all, or nearly all, of the dose was absorbed, and that the primary route of elimination of the parent drug and its metabolites is via the kidney. Renal elimination of unchanged drug accounts for approximately 15% to 20% of the administered dose.

Specific Populations

Hepatic Impairment

Hepatic impairment slows the elimination of LUCEMYRA but exhibits less effect on the peak plasma concentration following a single dose. In a study comparing the pharmacokinetics of LUCEMYRA (0.36 mg) in mild, moderate, and severe hepatically impaired subjects to subjects with normal hepatic function (6 subjects in each hepatic function group), mean Cmax values were similar for subjects with normal, mild, and moderate hepatic impairment as shown in Table 6.

Table 6: LUCEMYRA Pharmacokinetics in Subjects with Hepatic Impairment
 | Normal | Mild Impairment | Moderate Impairment | Severe Impairment
Child-Pugh Class & Score | Normal Function | Class A 5-6 | Class B 7-9 | Class C 10-15
Cmax % of normal | 100 | 114 | 117 | 166
AUClast % of normal | 100 | 127 | 190 | 304
AUC∞ % of normal | 100 | 117 | 185 | 260
t1/2 % of normal | 100 | 139 | 281 | 401

Renal Impairment

Renal impairment slows the elimination of LUCEMYRA but exhibits less effect on the peak plasma concentration following a single dose. In a study comparing the pharmacokinetics of LUCEMYRA (0.36 mg) in 8 end-stage renal disease subjects on 3 times weekly hemodialysis to 8 subjects with normal renal function matched for sex, age, and body mass index, mean Cmax values were similar for end-stage renal disease and normal renal function subjects, indicating no change in maximum LUCEMYRA exposure with renal impairment as shown in Table 7.

The impact of dialysis on the overall pharmacokinetics of LUCEMYRA during a typical 4-hour dialysis was minimal; the drop in LUCEMYRA plasma concentrations produced during the dialysis session was transient, with a rebound to nearly predialysis concentrations after re-equilibration within a few hours following completion of the dialysis cycle [see Dosage and Administration (2.3), Use in Specific Populations (8.7)].

In a study comparing the pharmacokinetics of LUCEMYRA (0.36 mg) in 6 subjects each with normal renal function, mild renal impairment, and moderate renal impairment as well as 5 subjects with severe renal impairment but not requiring dialysis, there were similar increases in mean Cmax values in subjects with mild and moderate renal impairment in comparison to subjects with normal renal function, with additional increases in mean Cmax values in subjects with severe renal impairment. Mean AUClast, AUC∞, and t1/2 increased with severity of renal impairment as shown in Table 7.

Table 7: LUCEMYRA Pharmacokinetics in Subjects with Renal Impairment
 | Normal | Mild Impairment | Moderate Impairment | Severe Impairment | ESRD or on dialysis
eGFR (mL/min/1.73 m^2) | ≥ 90 | 60-89 | 30-59 | 15-29 | < 15
Cmax % of normal | 100 | 124 | 117 | 154 | 104
AUClast % of normal | 100 | 157 | 187 | 272 | 181
AUC∞ % of normal | 100 | 144 | 173 | 243 | 171
t1/2 % of normal | 100 | 111 | 145 | 157 | 137

Drug Interaction Studies

LUCEMYRA coadministered with methadone

In a double-blind placebo-controlled study of 23 patients maintained on methadone (80 to 120 mg/day) concomitantly administered LUCEMYRA up to 2.88 mg/day, LUCEMYRA did not alter the pharmacokinetics of methadone. LUCEMYRA concentrations may be slightly increased when coadministered with methadone; however, the increase at concentrations expected with recommended dosing is not clinically meaningful [see Drug Interactions (7.1)].

LUCEMYRA coadministered with buprenorphine

In a double-blind placebo-controlled study of 30 subjects maintained on buprenorphine (16 to 24 mg/day) concomitantly administered LUCEMYRA up to 2.88 mg/day, no pharmacokinetic or pharmacodynamic interactions between LUCEMYRA and buprenorphine were seen.

LUCEMYRA coadministered with oral naltrexone

In an open-label, single-arm study of 24 healthy subjects, oral naltrexone (50 mg/day) did not significantly alter the single- dose pharmacokinetics of LUCEMYRA (0.36 mg). The alteration in steady-state pharmacokinetics of oral naltrexone was statistically significant in the presence of LUCEMYRA. The Tmax was delayed for both naltrexone and 6ß-naltrexol (2 to 3 hours), and overall exposure was slightly reduced when naltrexone was administered with LUCEMYRA [see Drug Interactions (7.2)].

LUCEMYRA coadministered with paroxetine

In an open-label, single-sequence study of 24 healthy subjects, the strong CYP2D6 inhibitor paroxetine (40 mg/day) increased LUCEMYRA (0.36 mg) Cmax and AUC∞ by approximately 11% and 28%, respectively [see Drug Interactions (7.4)].

13 NONCLINICAL TOXICOLOGY

13.1 Carcinogenesis, Mutagenesis, Impairment of Fertility

Carcinogenesis

No adequate long-term animal studies have been completed to evaluate the carcinogenic potential of lofexidine.

Mutagenesis

Lofexidine tested positive in the in vitro mouse lymphoma assay. Lofexidine tested negative in the in vitro bacterial reverse mutation assay (Ames assay) and in the in vivo rat micronucleus assay.

Impairment of Fertility

In a female fertility study in rabbits, fertility was not adversely impacted by administration of lofexidine hydrochloride up to 6.4 mg/kg/day (approximately 0.1 times the MRHD of 2.88 mg on an AUC basis) when administered orally starting 2 weeks prior to mating and through gestation and lactation. However, decreased breeding rate and higher post- implantation loss was observed at this dose, which correlated with higher resorptions and reduced litter size. Maternal toxicity, which included increased mortality rate, reduced body weight gain, and moderate sedation was observed at 6.4 mg/kg/day. The NOAEL for female fertility was 6.4 mg/kg/day and the NOAEL for female-mediated developmental parameters was 0.4 mg/kg/day (approximately 0.005 times the MRHD on an AUC basis).

In a fertility study in rats, fertility was unaffected by administration of lofexidine up to 0.88 mg/kg/day (approximately 0.2 times the MRHD on an AUC basis) via diet to male and female rats prior to mating and to the dams through gestation and lactation. No evidence of maternal toxicity was observed. However, no assessment of sperm or reproductive organs were performed in this study.

Reduced testes, epididymis, and seminiferous tubule weights, as well as delayed sexual maturation of males and females and decreases in the number of corpora lutea and implantations after mating, were noted in offspring of pregnant rats administered lofexidine hydrochloride orally from GD 6 through lactation at exposures less than the human exposure based on AUC comparisons.

14 CLINICAL STUDIES

Two randomized, double-blind, placebo-controlled trials supported the efficacy of LUCEMYRA.

Study 1, NCT01863186

Study 1 was a 2-part efficacy, safety, and dose-response study conducted in the United States in patients meeting DSM-IV criteria for opioid dependence who were physically dependent on short-acting opioids (e.g., heroin, hydrocodone, oxycodone). The first part of the study was an inpatient, randomized, double-blind, placebo-controlled design consisting of 7 days of inpatient treatment (Days 1 – 7) with LUCEMYRA 2.16 mg total daily dose (0.54 mg 4 times daily) (n=229), LUCEMYRA 2.88 mg total daily dose (0.72 mg 4 times daily) (n=222), or matching placebo (n=151). Patients also had access to a variety of support medications for withdrawal symptoms (guaifenesin, antacids, dioctyl sodium sulfosuccinate, psyllium hydrocolloid suspension, bismuth sulfate, acetaminophen, and zolpidem). The second part of the study (Days 8 – 14) was an open-label design where all patients who successfully completed Days 1 – 7 were eligible to receive open-label treatment with variable dose LUCEMYRA treatment (as determined by the investigator, but not to exceed 2.88 mg total daily dose) for up to an additional 7 days (Days 8 – 14) in either an inpatient or outpatient setting as determined by the investigator and the patient. No patient received LUCEMYRA for more than 14 days.

The two endpoints to support efficacy were the mean Short Opiate Withdrawal Scale of Gossop (SOWS-Gossop) total score on Days 1 – 7 of treatment and the proportion of patients who completed 7 days of treatment. The SOWS-Gossop, a patient-reported outcome (PRO) instrument, evaluates the following opioid withdrawal symptoms: feeling sick, stomach cramps, muscle spasms/twitching, feeling of coldness, heart pounding, muscular tension, aches and pains, yawning, runny eyes and insomnia/problems sleeping. For each opioid withdrawal symptom, patients are asked to rate their symptom severity using four response options (none, mild, moderate, and severe). The SOWS-Gossop total score ranges from 0 to 30, where a higher score indicates greater withdrawal symptom severity. The SOWS-Gossop was administered at baseline and once daily 3.5 hours after the first morning dose on Days 1 – 7.

Of the randomized and treated patients, 28% of placebo patients, 41% of LUCEMYRA 2.16 mg and 40% of LUCEMYRA 2.88 mg patients completed 7 days of treatment. The difference in proportion in both LUCEMYRA groups was significant compared to placebo. See Figure 1. Patients in the placebo group were more likely to drop out of the study prematurely due to lack of efficacy than patients treated with LUCEMYRA.

Figure 1: Completion of Treatment Period for Study 1

The mean SOWS-Gossop scores for Days 1 – 7 were 8.8, 6.5, and 6.1 for placebo, LUCEMYRA 2.16 mg and LUCEMYRA 2.88 mg, respectively. Results are shown in Figure 2. The mean difference between LUCEMYRA 2.16 mg and placebo was -2.3 with a 95% CI of (-3.4, -1.2). The mean difference between LUCEMYRA 2.88 mg and placebo was -2.7 with a 95% CI of (-3.9, -1.6). They were both significant. Symptoms assessed on the SOWS-Gossop were recorded as absent or mild for almost all patients remaining to the end of the assessment period.

Figure 2: Mean SOWS-Gossop Scores for Days 1 – 7 in Study 1

Study 2, NCT00235729

Study 2 was an inpatient, randomized, multicenter, double-blind, placebo-controlled study carried out in the United States in patients meeting DSM-IV criteria for opioid dependence who were physically dependent on short-acting opioids (e.g., heroin, hydrocodone, oxycodone). Patients were treated with LUCEMYRA tablets (2.88 mg/day [0.72 mg 4 times daily]) or matching placebo for 5 days (Days 1 – 5). Patients also had access to a variety of support medications for withdrawal symptoms (guaifenesin, antacids, dioctyl sodium sulfosuccinate, psyllium hydrocolloid suspension, bismuth sulfate, acetaminophen, and zolpidem). All patients then received placebo on Days 6 and 7 and were discharged on Day 8.

The two endpoints to support efficacy were the mean SOWS-Gossop total score on Days 1 – 5 of treatment and the proportion of patients who completed 5 days of treatment. The SOWS-Gossop was administered at baseline and once daily 3.5 hours after the first morning dose on Days 1 – 5.

A total of 264 patients were randomized into the study. Of these, 134 patients were randomized to LUCEMYRA 2.88 mg/day and 130 patients to placebo.

Of the randomized and treated patients, 33% of placebo patients and 49% of LUCEMYRA patients completed 5 days of treatment. The difference in proportion between the two groups was significant. See Figure 3. Patients in the placebo group were more likely to drop out of the study prematurely due to lack of efficacy than patients treated with LUCEMYRA.

Figure 3: Completion of Treatment Period in Study 2

The mean SOWS-Gossop scores for Days 1 – 5 were 8.9 and 7.0 for placebo and LUCEMYRA 2.88 mg, respectively. Results are shown in Figure 4. The mean difference was -1.9 with a 95% CI of (-3.2, -0.6) and was statistically significant.

Figure 4: Mean SOWS-Gossop Scores for Days 1 – 5 in Study 2

16 HOW SUPPLIED/STORAGE AND HANDLING

How Supplied

Available as 0.18 mg round, convex-shaped, peach colored, film-coated tablets, imprinted with "LFX" on one side and "18" on the other side; approximately 7 mm in diameter.

Bottles of 36 tablets | NDC 78670-050-36
Bottles of 96 tablets | NDC 78670-050-96

Storage

Store in original container at controlled room temperature, 25°C (77°F); with excursions permitted between 15°C to 30°C (59°F to 86°F) [see USP Controlled Room Temperature]. Keep LUCEMYRA away from excess heat and moisture both in the pharmacy and after dispensing. Do not remove desiccant packs from bottles until all tablets are used. Keep LUCEMYRA and all medicines out of the reach of children.

17 PATIENT COUNSELING INFORMATION

Advise patients to read the FDA-approved patient labeling (Patient Information).

LUCEMYRA may mitigate, but not completely prevent, the symptoms associated with opioid withdrawal syndrome, which may include feeling sick, stomach cramps, muscle spasms or twitching, feeling of cold, heart pounding, muscular tension, aches and pains, yawning, runny eyes and sleep problems (insomnia). Patients should be advised that withdrawal will not be easy. Additional supportive measures should be clearly advised, as needed.

Hypotension and Bradycardia

Inform patients to be alert for any symptoms of low blood pressure or pulse (e.g., dizziness, lightheadedness, or feelings of faintness at rest or upon abruptly standing). Advise patients on how to reduce the risk of serious consequences should hypotension occur (sit or lie down, carefully rise from a sitting or lying position).

Patients being given LUCEMYRA in an outpatient setting should be capable of and instructed on self-monitoring for hypotension, orthostasis, and bradycardia and advised to withhold LUCEMYRA doses and contact their healthcare provider for instructions if they experience these signs or related symptoms [see Warnings and Precautions (5.1)].

Advise patients to avoid becoming dehydrated or overheated, which may potentially increase the risks of hypotension and syncope [see Warnings and Precautions (5.1)].

Concomitant Medications

Review with patients all concomitant medications being taken and request that they immediately inform their healthcare provider of any changes in concomitant medications, including any other medications that may be used to treat individual symptoms of withdrawal.

Increased Risk of CNS Depression with Concomitant use of CNS Depressant Drugs

Inform patients of the increased risk of CNS depression with concomitant use of benzodiazepines, alcohol, barbiturates, or other sedating drugs [see Warnings and Precautions (5.3)].

Advise patients using LUCEMYRA in an outpatient setting that, until they learn how they respond to LUCEMYRA, they should be careful or avoid doing activities such as driving or operating heavy machinery.

Sudden Discontinuation of LUCEMYRA

Inform patients not to discontinue LUCEMYRA without consulting their healthcare provider [see Warnings and Precautions (5.5)].

Risk of Opioid Overdose After Discontinuation of Opioids

Advise patients that after a period of not using opioid drugs, they may be more sensitive to the effects of opioids and at greater risk of overdosing [see Warnings and Precautions (5.4)].

This product's Prescribing Information may have been updated. For current full Prescribing Information, please visit www.usworldmeds.com.

Distributed by:
USWM, LLC 4441 Springdale Road
Louisville, KY 40241

Under License from Britannia Pharmaceuticals Limited.

USWM, LLC is the exclusive licensee and distributor of LUCEMYRA® in the United States and Its territories. ©2020. LUCEMYRA® is a registered trademark of USWM, LLC.

360-10020.01

PATIENT INFORMATION
LUCEMYRA® (LEW-sem-EER-uh)
(lofexidine) tablets

What is the most important information I should know about LUCEMYRA and discontinuing opioid drugs?

LUCEMYRA can cause serious side effects, including low blood pressure (hypotension), slow heart rate (bradycardia), and fainting.

If you have any of the following signs or symptoms, tell your healthcare provider right away:

- low blood pressure
- slow heartbeat
- dizziness

- lightheadedness
- feeling faint at rest or when standing up

If you take LUCEMYRA at home and have any of these signs and symptoms, do not take your next dose of LUCEMYRA until you have talked to your healthcare provider. You should avoid becoming dehydrated or overheated during treatment with LUCEMYRA, which may increase your risk of low blood pressure and fainting. You should also be careful not to stand up too suddenly from lying down or sitting.

When your treatment is complete you will need to stop taking LUCEMYRA gradually or your blood pressure could increase. For more information about side effects, see "What are the possible side effects of LUCEMYRA?"

Increased risk of opioid overdose. After a period of time of not using opioid drugs, you can become more sensitive to the effects of opioids if you start using opioids again. This may increase your risk of overdose and death.

What is LUCEMYRA?

LUCEMYRA is a non-opioid prescription medicine used in adults to help with the symptoms of opioid withdrawal that may happen when you stop taking an opioid suddenly.

LUCEMYRA will not completely prevent the symptoms of opioid withdrawal, which may include feeling sick, stomach cramps, muscle spasms or twitching, feeling of cold, heart pounding, muscular tension, aches and pains, yawning, runny eyes and sleep problems (insomnia).

LUCEMYRA is not a treatment for opioid use disorder. If you have been diagnosed with opioid use disorder (opioid addiction), your healthcare provider may prescribe LUCEMYRA as part of a complete treatment program for your opioid use disorder (opioid addiction).

It is not known if LUCEMYRA is safe and effective in children.

Before taking LUCEMYRA, tell your healthcare provider about all of your medical conditions, including if you:

- have low blood pressure
- have a slow heart rate
- have any heart problems, including history of heart attack or a condition called long QT syndrome
- have liver or kidney problems
- drink alcohol
- are pregnant or plan to become pregnant. It is not known if LUCEMYRA can harm your unborn baby.
- are breastfeeding or plan to breastfeed. It is not known if LUCEMYRA passes into your breast milk. Talk to your healthcare provider about the best way to feed your baby during treatment with LUCEMYRA.

Tell your healthcare provider about all of the medicines you take, including prescription and over-the-counter medicines, vitamins, herbal supplements, and any medications you may take for the individual symptoms of opioid withdrawal (such as pain relievers or medications for upset stomach).

Especially tell your healthcare provider if you take benzodiazepines, barbiturates, tranquilizers, or sleeping pills. Taking LUCEMYRA with these medicines can cause serious side effects. Ask your healthcare provider or pharmacist if you are not sure if you are taking any of these medicines.

How should I take LUCEMYRA?

- Take LUCEMYRA exactly as your healthcare provider tells you to take it.
- Your healthcare provider may change your dose if needed.
- Do not change your dose or stop taking LUCEMYRA without talking to your healthcare provider.
- Take LUCEMYRA with or without food.
- If you take too much LUCEMYRA, go to the nearest hospital emergency room right away.

What should I avoid while taking LUCEMYRA?

Do not drive, operate heavy machinery, or perform any other dangerous activities until you know how LUCEMYRA affects you.

What are the possible side effects of LUCEMYRA?

The most common side effects of LUCEMYRA include:

- low blood pressure or symptoms of low blood pressure such as lightheadedness
- slow heart rate

- dizziness
- sleepiness
- dry mouth

These are not all the possible side effects of LUCEMYRA.

Call your healthcare provider for medical advice about side effects. You may report side effects to FDA at 1-800-FDA-1088. You may also report side effects to US WorldMeds at 1-833-LUCEMYRA.

How should I store LUCEMYRA?

- Store LUCEMYRA at room temperature between 68°F to 77°F (20°C to 25°C).
- Keep LUCEMYRA in its original container.
- Keep LUCEMYRA away from heat and moisture.
- LUCEMYRA bottles contain desiccant packs to help keep the tablets dry. Do not remove the desiccant packs until all the tablets are used.

Keep LUCEMYRA and all medicines out of the reach of children.

General information about the safe and effective use of LUCEMYRA.

Medicines are sometimes prescribed for purposes other than those listed in a Patient Information leaflet. Do not use LUCEMYRA for a condition for which it was not prescribed. Do not give LUCEMYRA to other people, even if they have the same symptoms that you have. It may harm them. You can ask your pharmacist or healthcare provider for information about LUCEMYRA that is written for health professionals.

What are the ingredients of LUCEMYRA?

Active ingredient: lofexidine.

Inactive ingredients: lactose, citric acid, povidone, microcrystalline cellulose, calcium stearate, sodium lauryl sulphate, and Opadry OY S 9480 (contains indigo carmine and sunset yellow).

Distributed by: USWM, LLC, 4441 Springdale Road, Louisville, KY 40241

Under License from Britannia Pharmaceuticals Limited.
USWM, LLC is the exclusive licensee and distributor of LUCEMYRA® in the United States and Its territories.
©2020. LUCEMYRA® is a registered trademark of USWM, LLC.
For more information, go to www.LUCEMYRA.com or call 1-833-LUCEMYRA

This Patient Information has been approved by the U.S. Food and Drug Administration.
360-10020.01

Issued: 09/2020

PRINCIPAL DISPLAY PANEL - 0.18 mg Tablet Bottle Carton

Rx only
NDC 78670-050-96

Lucemyra®
(lofexidine) tablets

0.18 mg

Store and dispense
in original container.

Protect from heat and moisture.
Do not remove desiccants.
Keep the bottle tightly closed.

Keep out of reach of children.
96 tablets

US WorldMeds®